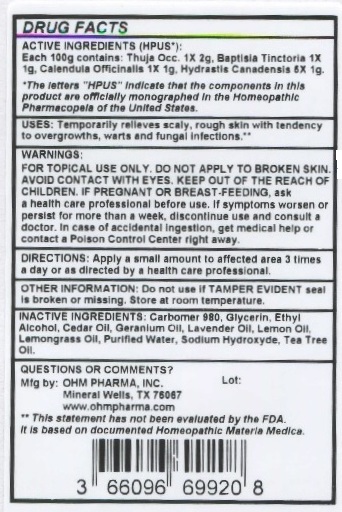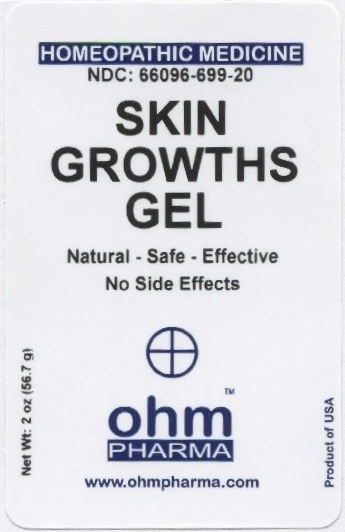 DRUG LABEL: OHM Skin Growths
NDC: 66096-699 | Form: GEL
Manufacturer: OHM PHARMA INC.
Category: homeopathic | Type: HUMAN OTC DRUG LABEL
Date: 20211229

ACTIVE INGREDIENTS: THUJA OCCIDENTALIS LEAFY TWIG 1 [hp_X]/56.7 g; BAPTISIA TINCTORIA ROOT 1 [hp_X]/56.7 g; CALENDULA OFFICINALIS FLOWERING TOP 1 [hp_X]/56.7 g; GOLDENSEAL 5 [hp_X]/56.7 g
INACTIVE INGREDIENTS: CARBOMER 980; GLYCERIN; ALCOHOL; CEDAR LEAF OIL; GERANIUM OIL, ALGERIAN TYPE; LAVENDER OIL; LEMON OIL; WEST INDIAN LEMONGRASS OIL; WATER; SODIUM HYDROXIDE; TEA TREE OIL

OHM Skin Growths Gel

ACTIVE INGREDIENT

ACTIVE INGREDIENTS (HPUS*): Each 100g contains: Thuja Occ. 1X 2g, Baptisia Tinctoria 1X 1g, Calendula Officinalis 1X 1g, Hydrastis Canadensis 5X 1g.

* The letters "HPUS" indicate that the components in this product are officially monographed in the Homeopathic Pharmacopeia of the United States.

INDICATIONS AND USAGE

Uses: Temporarily relieves scaly, rough skin with tendency to overgrowths, warts and fungal infections.**

**This statement has not been evaluated by the FDA. It is based on documented Homeopathic Materia Medica.

WARNINGS

WARNINGS: FOR TOPICAL USE ONLY. DO NOT APPLY TO BROKEN SKIN. AVOID CONTACT WITH EYES. IF PREGNANT OR BREAST-FEEDING, ask a health care professional before use. If symptoms worsen or persist for more than a week, discontinue use and consult a doctor. In case of accidental ingestion, get medical help or contact a Poison Control Center right away.

- KEEP OUT OF REACH OF CHILDREN.

DOSAGE AND ADMINISTRATION

DIRECTIONS: Apply a small amount to affected area 3 times a day or as directed by a health care professional.

OTHER INFORMATION: Do not use if TAMPER EVIDENT seal is broken or missing. Store at room temperature.

INACTIVE INGREDIENT

INACTIVE INGREDIENTS: Carbomer 980, Glycerin, Ethyl Alcohol, Cedar Oil, Geranium Oil, Lavender Oil, Lemon Oil, Lemongrass Oil, Purified Water, Sodium Hydroxide, Tea Tree Oil.

QUESTIONS OR COMMENTS? Mfg. By: OHM PHARMA, INC. Mineral Wells, TX 76067

www.ohmpharma.com

PACKAGE LABEL

HOMEOPATHIC MEDICINE

NDC: 66096-699-20

SKIN GROWTHS GEL

Natural - Safe - Effective

No Side Effects

Net Wt: 2 oz (56.7 g)

Product of USA

PURPOSE

Relieves scaly, rough skin.